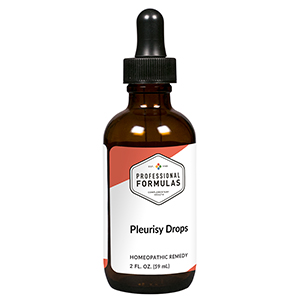 DRUG LABEL: Pleurisy Drops
NDC: 63083-2047 | Form: LIQUID
Manufacturer: Professional Complementary Health Formulas
Category: homeopathic | Type: HUMAN OTC DRUG LABEL
Date: 20190815

ACTIVE INGREDIENTS: ASCLEPIAS TUBEROSA FLOWERING TOP 3 [hp_X]/59 mL; CINCHONA OFFICINALIS BARK 6 [hp_X]/59 mL; BEEF LUNG 6 [hp_X]/59 mL; RANUNCULUS BULBOSUS WHOLE 6 [hp_X]/59 mL; SEPIA OFFICINALIS JUICE 6 [hp_X]/59 mL; PICRIC ACID 8 [hp_X]/59 mL; ARSENIC TRIIODIDE 30 [hp_X]/59 mL; BRYONIA ALBA ROOT 30 [hp_X]/59 mL; OYSTER SHELL CALCIUM CARBONATE, CRUDE 30 [hp_X]/59 mL; LYCOPODIUM CLAVATUM SPORE 30 [hp_X]/59 mL; PHOSPHORUS 30 [hp_X]/59 mL; SILICON DIOXIDE 30 [hp_X]/59 mL
INACTIVE INGREDIENTS: ALCOHOL; WATER

C47

ACTIVE INGREDIENTS

Asclepias tuberosa 3X
Cinchona officinalis 6X
Lung 6X
Ranunculus bulbosus 6X
Sepia 6X
Picricum acidum 8X
Arsenicum iodatum 30X
Bryonia 30X
Calcarea carbonica 30X
Lycopodium clavatum 30X
Phosphorus 30X
Silicea 30X

QUESTIONS

Professional Formulas

PO Box 2034 Lake Oswego, OR 97035

INDICATIONS

For temporary relief of mild pain in chest when breathing, sneezing, or coughing, shortness of breath, or dry cough.*

PURPOSE

*Claims based on traditional homeopathic practice, not accepted medical evidence. Not FDA evaluated.

WARNINGS

Persistent symptoms may be a sign of a serious condition. Consult a doctor immediately if you experience unexplained intense chest pain while breathing. Keep out of the reach of children. In case of overdose, get medical help or contact a poison control center right away. If pregnant or breastfeeding, ask a healthcare professional before use.

Keep out of the reach of children.

PREGNANCY OR BREAST FEEDING

If pregnant or breastfeeding, ask a healthcare professional before use.

DIRECTIONS

Place drops under tongue 30 minutes before/after meals. Adults and children 12 years and over: Take 10 drops up to 3 times per day. Consult a physician for use in children under 12 years of age.

OTHER INFORMATION

Tamper resistant. If seal is broken, do not use. After opening, close container tightly and store at room temperature away from heat.

INACTIVE INGREDIENTS

20% ethanol, purified water.

LABEL

Est 1985

Professional Formulas

Complementary Health

Pleurisy Drops

Homeopathic Remedy

2 FL. OZ. (59 mL)